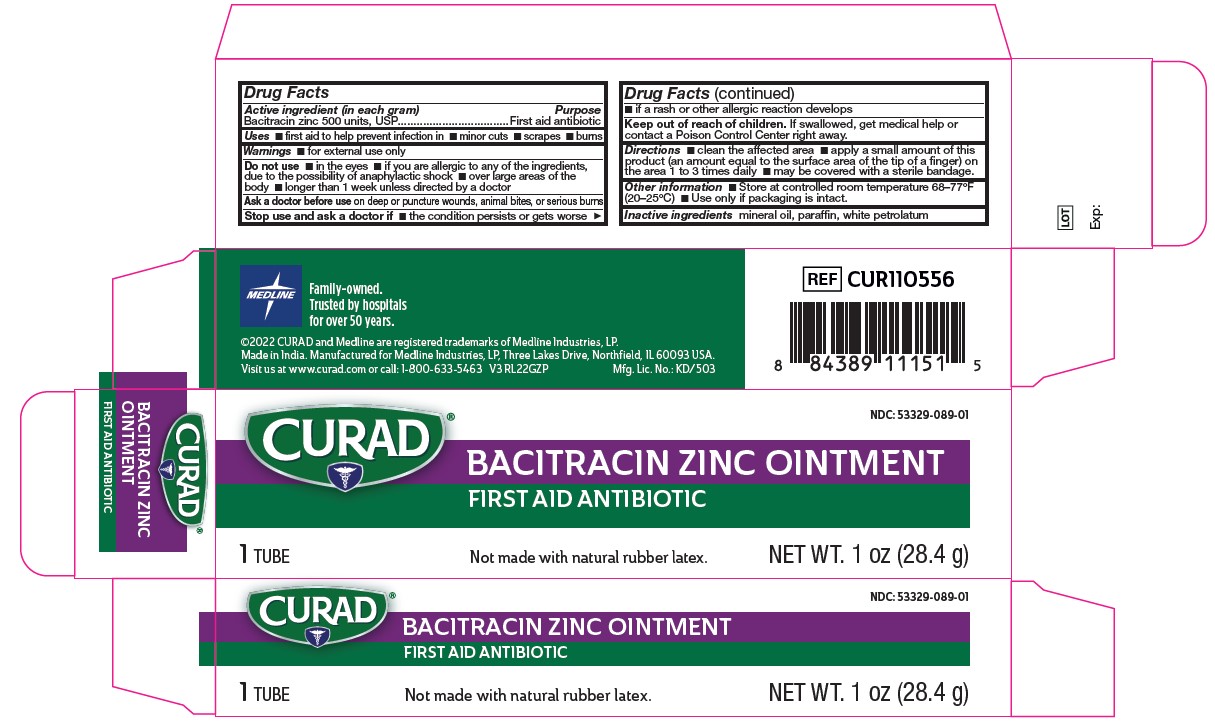 DRUG LABEL: First Aid Antibiotic
NDC: 53329-089 | Form: OINTMENT
Manufacturer: Medline Industries, LP
Category: otc | Type: HUMAN OTC DRUG LABEL
Date: 20251009

ACTIVE INGREDIENTS: BACITRACIN ZINC 500 [USP'U]/1 g
INACTIVE INGREDIENTS: MINERAL OIL; WHITE PETROLATUM; PARAFFIN

089 Curad Bacitracin Zinc Ointment

Active ingredient (in each gram)

Bacitracin Zinc 500 units, USP

Purpose

First aid antibiotic

Uses

First aid to help prevent infection in

- minor cuts
- scrapes
- burns

Warnings

- For external use only

Do not use

- in the eyes
- if you are allergic to any of the ingredients, due to the possibility of anaphylactic shock
- over large areas of the body
- longer than 1 week unless directed by a doctor

Ask a doctor before use

on deep or puncture wounds, animal bites, or serious burns

Stop use and ask a doctor if

- the condition persists or gets worse
- if a rash or other allergic reaction occurs

Keep out of reach of children.

If swallowed, get medical help or contact a Poison Control Center right away.

Directions

- Clean the affected area.
- Apply a small amount of this product (an amount equal to the surface area of the tip of a finger) on the area 1 to 3 times daily.
- May be covered with a sterile bandage.

Other information

- store at controlled room temperature 68º-77ºF (20º-25ºC)
- Use only if packaging is intact.

Inactive ingredients

mineral oil, paraffin, white petrolatum

Manufacturing Information

Made in India.

Manufactured for Medline Industries, LP

Three Lakes Drive, Northfield, IL 60093 USA

Visit us at www.curad.com or call: 1-800-633-5463

REF: CUR110556

V3 RL22GZP

RECENT MAJOR CHANGES

- Warnings and Precautions